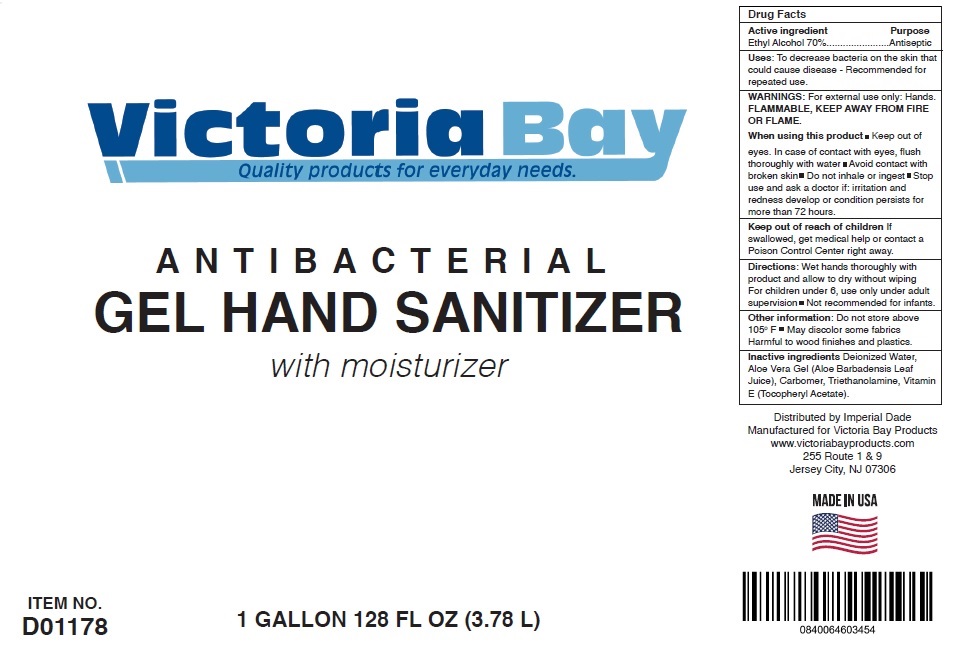 DRUG LABEL: Victoria Bay Gel Hand Sanitizer
NDC: 71907-100 | Form: GEL
Manufacturer: Dade Paper & Bag, Llc
Category: otc | Type: HUMAN OTC DRUG LABEL
Date: 20200730

ACTIVE INGREDIENTS: ALCOHOL 70 L/100 L
INACTIVE INGREDIENTS: WATER; ALOE VERA LEAF; CARBOMER HOMOPOLYMER, UNSPECIFIED TYPE; TROLAMINE; .ALPHA.-TOCOPHEROL

Victoria Bay GEL HAND SANITIZER

Active ingredient

Ethyl Alcohol 70%

Purpose

Antiseptic

Uses:

To decrease bacteria on the skin that could cause disease - Recommended for repeated use.

WARNINGS:

For external use only: Hands.

FLAMMABLE, KEEP AWAY FROM FIRE OR FLAME.

When using this product ■ Keep out of eyes. In case of contact with eyes, flush thoroughly with water ■ Avoid contact with broken skin ■ Do not inhale or ingest ■ Stop use and ask a doctor if: irritation and redness develop or condition persists for more than 72 hours.

Keep out of reach of children If swallowed, get medical help or contact a Poison Control Center right away.

Directions:

Wet hands thoroughly with product and allow to dry without wiping
For children under 6, use only under adult supervision ■ Not recommended for infants.

Other information:

Do not store above 105°F ■ May discolor some fabrics
Harmful to wood finishes and plastics.

Inactive ingredients

Deionized Water, Aloe Vera Gel (Aloe Barbadensis Leaf Juice), Carbomer, Triethanolamine, Vitamin E (Tocopheryl Acetate).

Quality products for everyday needs.

ANTIBACTERIAL

with moisturizer

Distributed by Imperial Dade

Manufactured for Victoria Bay Products

www.victoriabayproducts.com

255 Route 1 & 9

Jersey City, NJ 07306

MADE IN USA